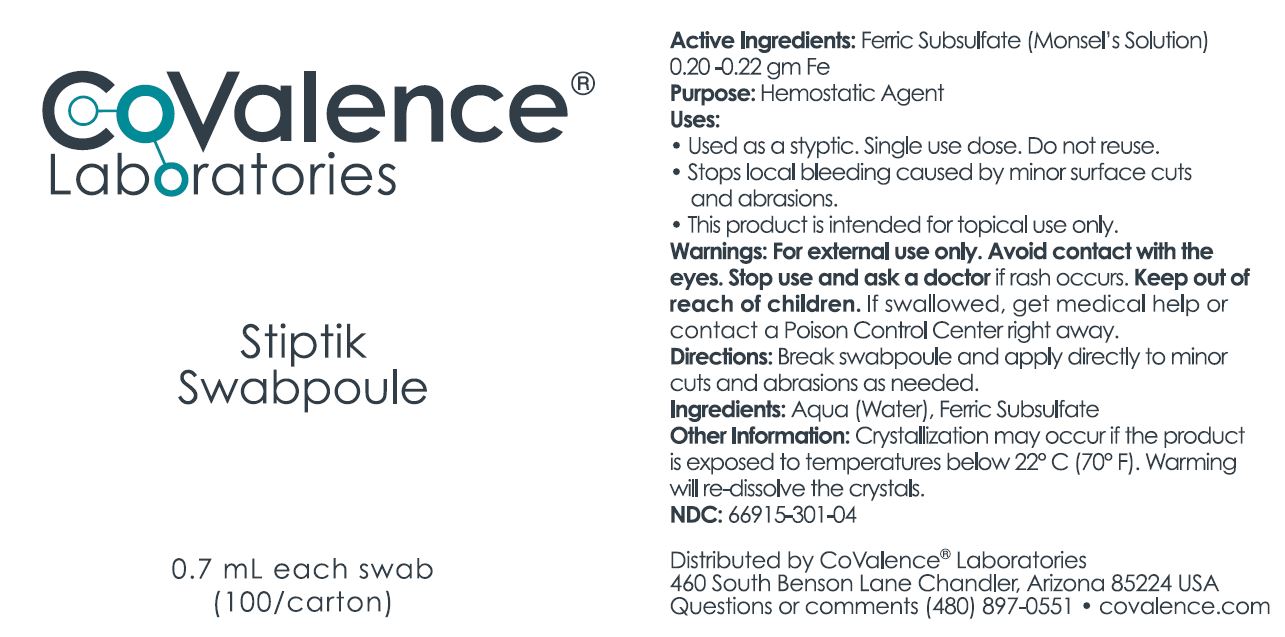 DRUG LABEL: Stiptik
NDC: 66915-301 | Form: SOLUTION
Manufacturer: Island Kinetics, Inc. d.b.a. CoValence Laboratories
Category: prescription | Type: HUMAN PRESCRIPTION DRUG LABEL
Date: 20220105

ACTIVE INGREDIENTS: FERRIC SUBSULFATE 1 g/1 g
INACTIVE INGREDIENTS: WATER

HIGHLIGHTS OF PRESCRIBING INFORMATION

OTC #301; Stiptik Swab (100)
These highlights do not include all the information needed to use see full prescribing information for Initial U.S. Approval.

DOSAGE & ADMINISTRATION SECTION

Active Ingredients: Ferric Subsulfate (Monsel's Solution) 0.20 - 0.22 gm Fe

Purpose: Hemostatic Agent

Uses:

- Used as a styptic. Single use dose. Do not resuse.
- Stops local bleeding cause by minor surface cuts and abrasions.
- This proudct is intended for topical use only.

Warnings: For exernal use only. Avoid contact with the eyes. Stop use and ask a doctor if rash occurs. Keep out of reach of children. If swallowed, get medical help or contact a Poison Control Center right away.

Directions: Break swabpoule and apply directly to minor cuts and abraisons as needed.

Ingredients: Aqua (Water), Ferric Subsulfate

Other information: Crystallization may occur if the product is exposed to temperatures below 22° C (70° F). Warming will re-dissolve the crystals.

NDC: 66915-301-04

FULL PRESCRIBING INFORMATION